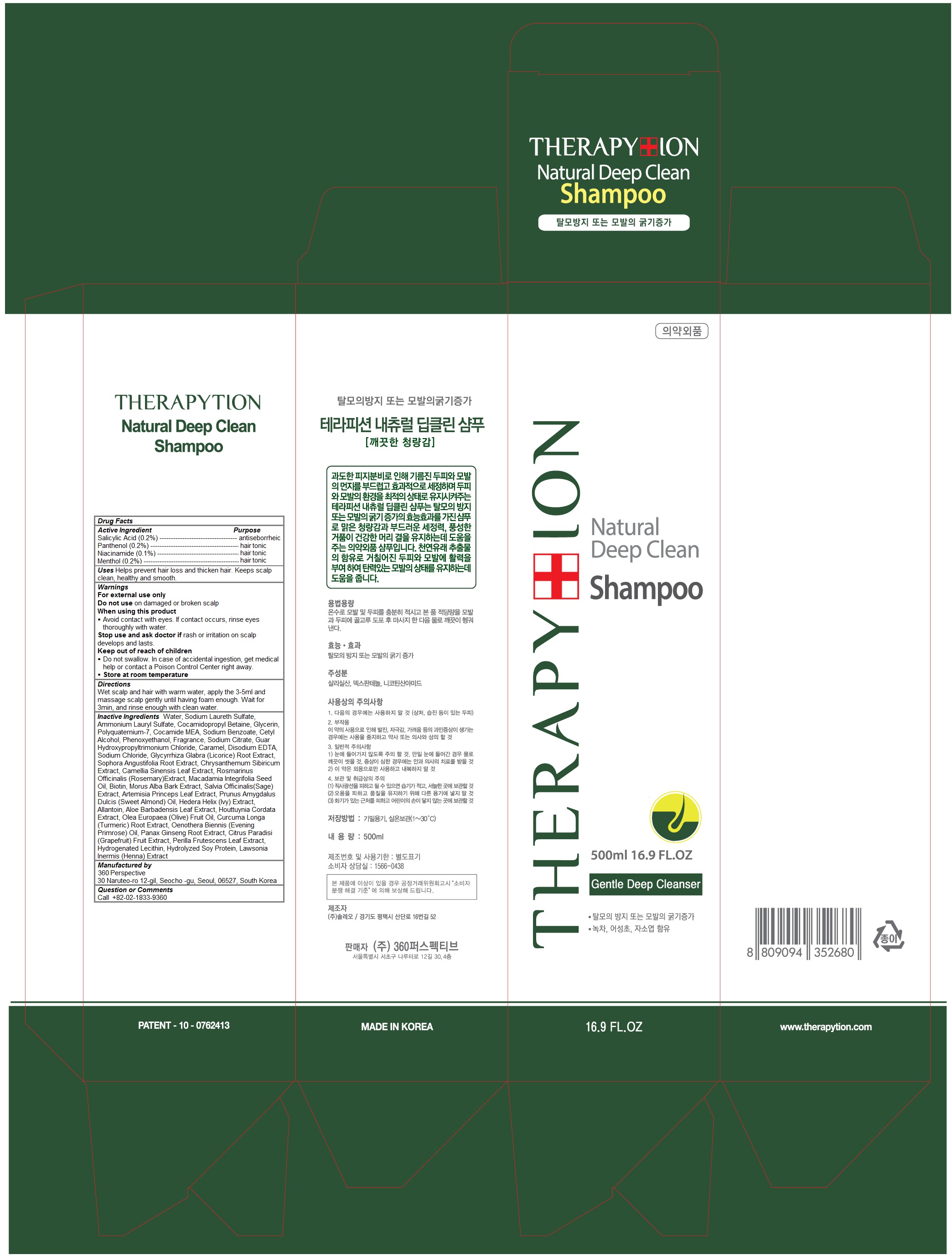 DRUG LABEL: Therapytion Natural Deep Clean
NDC: 70477-104 | Form: SHAMPOO
Manufacturer: 360 Perspective
Category: otc | Type: HUMAN OTC DRUG LABEL
Date: 20160420

ACTIVE INGREDIENTS: Panthenol 0.002 1/500 mL; Salicylic Acid 0.002 1/500 mL; Niacinamide 0.001 1/500 mL; Menthol 0.002 1/500 mL
INACTIVE INGREDIENTS: water; Sodium Laureth Sulfate; Ammonium Lauryl Sulfate; Cocamidopropyl Betaine; Glycerin; POLYQUATERNIUM-7 (70/30 ACRYLAMIDE/DADMAC; 1600000 MW); COCO MONOETHANOLAMIDE; SODIUM BENZOATE; CETYL ALCOHOL; PHENOXYETHANOL; GUAR HYDROXYPROPYLTRIMONIUM CHLORIDE (1.7 SUBSTITUENTS PER SACCHARIDE); SODIUM CITRATE, UNSPECIFIED FORM; Caramel; EDETATE DISODIUM; SODIUM CHLORIDE; GLYCYRRHIZA GLABRA; SOPHORA FLAVESCENS ROOT; GREEN TEA LEAF; ROSEMARY; MACADAMIA OIL; BIOTIN; MORUS ALBA BARK; SALVIA OFFICINALIS ROOT; ARTEMISIA PRINCEPS LEAF; ALMOND OIL; HEDERA HELIX LEAF; Allantoin; ALOE VERA LEAF; HOUTTUYNIA CORDATA FLOWERING TOP; OLIVE OIL; TURMERIC; EVENING PRIMROSE OIL; ASIAN GINSENG; GRAPEFRUIT; PERILLA FRUTESCENS TOP; HYDROGENATED SOYBEAN LECITHIN; HYDROLYZED SOY PROTEIN (ENZYMATIC; 2000 MW)

Therapytion Natural Deep Clean Shampoo